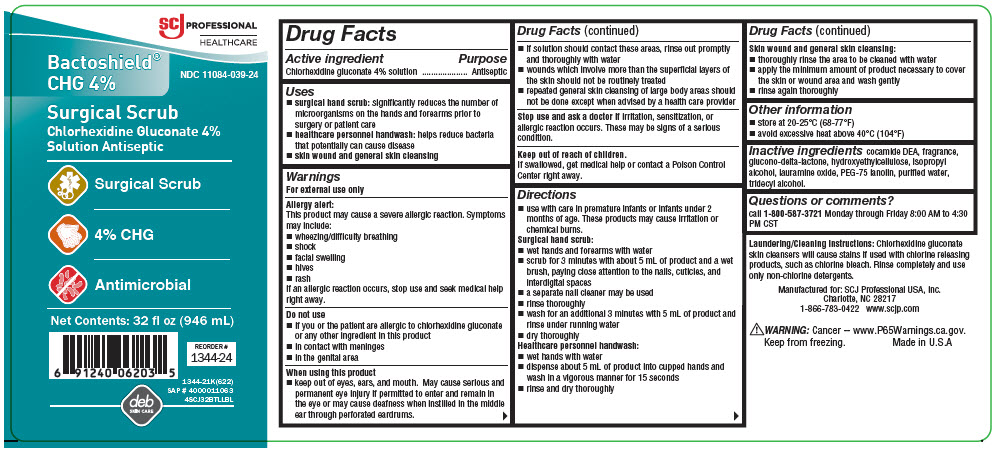 DRUG LABEL: Bactoshield CHG
NDC: 11084-039 | Form: SOLUTION
Manufacturer: SC Johnson Professional USA, Inc.
Category: otc | Type: HUMAN OTC DRUG LABEL
Date: 20221128

ACTIVE INGREDIENTS: CHLORHEXIDINE GLUCONATE 40 mg/1 mL
INACTIVE INGREDIENTS: COCO DIETHANOLAMIDE; GLUCONOLACTONE; HYDROXYETHYL CELLULOSE (5000 MPA.S AT 1%); ISOPROPYL ALCOHOL; LAURAMINE OXIDE; PEG-75 LANOLIN; WATER; TRIDECYL ALCOHOL

Bactoshield CHG

Drug Facts

Active ingredient

Chlorhexidine gluconate 4% solution

Purpose

Antiseptic

Uses

- surgical hand scrub: significantly reduces the number of microorganisms on the hands and forearms prior to surgery or patient care
- healthcare personnel handwash: helps reduce bacteria that potentially can cause disease
- skin wound and general skin cleansing

Warnings

For external use only

Allergy alert

This product may cause a severe allergic reaction. Symptoms may include:

- wheezing/difficulty breathing
- shock
- facial swelling
- hives
- rash

If an allergic reaction occurs, stop use and seek medical help right away.

Do not use

- if you or the patient are allergic to chlorhexidine gluconate or any other ingredient in this product
- in contact with meninges
- in the genital area

When using this product

- keep out of eyes, ears, and mouth. May cause serious and permanent eye injury if permitted to enter and remain in the eye or may cause deafness when instilled in the middle ear through perforated eardrums.
- if solution should contact these areas, rinse out promptly and thoroughly with water
- wounds which involve more than the superficial layers of the skin should not be routinely treated
- repeated general skin cleansing of large body areas should not be done except when advised by a health care provider

Stop use and ask a doctor if irritation, sensitization, or allergic reaction occurs. These may be signs of a serious condition.

Keep out of reach of children.

If swallowed, get medical help or contact a Poison Control Center right away.

Directions

- use with care in premature infants or infants under 2 months of age. These products may cause irritation or chemical burns.

Surgical hand scrub

- wet hands and forearms with water
- scrub for 3 minutes with about 5 mL of product and a wet brush, paying close attention to the nails, cuticles, and interdigital spaces
- a separate nail cleaner may be used
- rinse thoroughly
- wash for an additional 3 minutes with 5 mL of product and rinse under running water
- dry thoroughly

Healthcare personnel handwash

- wet hands with water
- dispense about 5 mL of product into cupped hands and wash in a vigorous manner for 15 seconds
- rinse and dry thoroughly

Skin wound and general skin cleansing

- thoroughly rinse the area to be cleaned with water
- apply the minimum amount of product necessary to cover the skin or wound area and wash gently
- rinse again thoroughly

Other information

- store at 20-25°C (68-77°F)
- avoid excessive heat above 40°C (104°F)

Inactive ingredients

cocamide DEA, fragrance, glucono-delta-lactone, hydroxyethylcellulose, isopropyl alcohol, lauramine oxide, PEG-75 lanolin, purified water, tridecyl alcohol.

Questions or comments?

call 1-800-587-3721 Monday through Friday 8:00 AM to 4:30 PM CST

PRINCIPAL DISPLAY PANEL - 946 mL Bottle Label

SCJ PROFESSIONAL
HEALTHCARE

Bactoshield®
CHG 4%

NDC 11084-039-24

Surgical Scrub
Chlorhexidine Gluconate 4%
Solution Antiseptic

Surgical Scrub

4% CHG

Antimicrobial

Net Contents: 32 fl oz (946 mL)

REORDER #
1344-24

1344-21K(622)
SAP # 4000011063
4SCJ32BTLLBL

deb
SKIN CARE